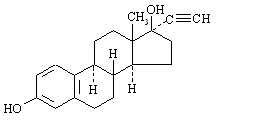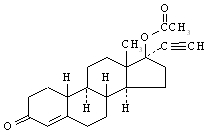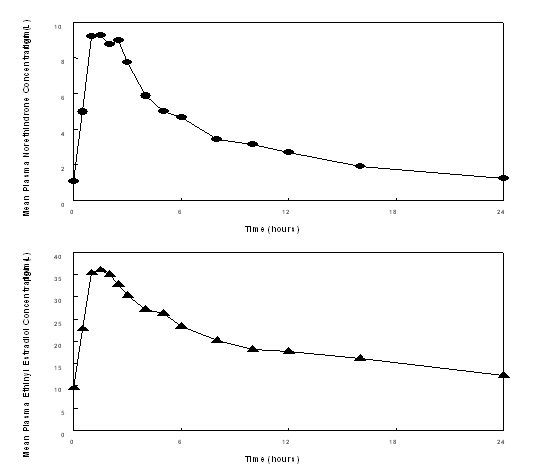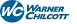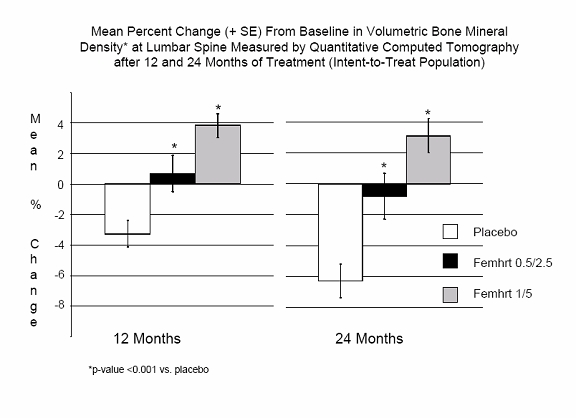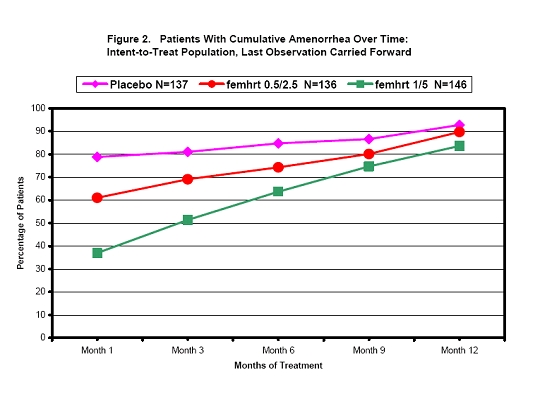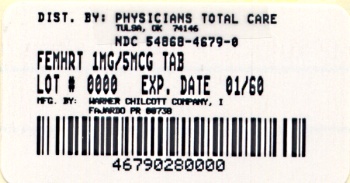 DRUG LABEL: femhrt
NDC: 54868-4679 | Form: TABLET
Manufacturer: Physicians Total Care, Inc.
Category: prescription | Type: HUMAN PRESCRIPTION DRUG LABEL
Date: 20081002

ACTIVE INGREDIENTS: NORETHINDRONE ACETATE 1 mg/1 1; ETHINYL ESTRADIOL 5 ug/1 1
INACTIVE INGREDIENTS: CALCIUM STEARATE; LACTOSE MONOHYDRATE; CELLULOSE, MICROCRYSTALLINE; STARCH, CORN

femhrt® (norethindrone acetate/ethinyl estradiol tablets)

WARNING

Estrogens and progestins should not be used for the prevention of cardiovascular disease or dementia. (See WARNINGS, Cardiovascular disorders and Dementia.)

The Women’s Health Initiative (WHI) study reported increased risks of myocardial infarction, stroke, invasive breast cancer, pulmonary emboli, and deep vein thrombosis in postmenopausal women (50 to 79 years of age) during 5 years of treatment with oral conjugated estrogens (CE 0.625 mg) combined with medroxyprogesterone acetate (MPA 2.5 mg) relative to placebo. (See CLINICAL PHARMACOLOGY, Clinical Studies and WARNINGS, Cardiovascular disorders and Malignant neoplasms, Breast cancer.)

The Women’s Health Initiative Memory Study (WHIMS), a substudy of WHI, reported increased risk of developing probable dementia in postmenopausal women 65 years of age or older during 4 years of treatment with oral conjugated estrogens plus medroxyprogesterone acetate relative to placebo. It is unknown whether this finding applies to younger postmenopausal women. (See CLINICAL PHARMACOLOGY, Clinical Studies, WARNINGS, Dementia and PRECAUTIONS, Geriatric Use.)

Other doses of oral conjugated estrogens with medroxyprogesterone acetate, and other combinations and dosage forms of estrogens and progestins were not studied in the WHI clinical trials and, in the absence of comparable data, these risks should be assumed to be similar. Because of these risks, estrogens with or without progestins should be prescribed at the lowest effective doses and for the shortest duration consistent with treatment goals and risks for the individual woman.

DESCRIPTION

femhrt® (norethindrone acetate/ethinyl estradiol tablets) is a continuous dosage regimen of a progestin-estrogen combination for oral administration.

The following two strengths of femhrt tablets are available:

femhrt (0.5 mg/2.5 mcg): Each white oval tablet contains 0.5 mg norethindrone acetate and 2.5 mcg ethinyl estradiol.

femhrt (1 mg/5 mcg): Each white D-shaped tablet contains 1 mg norethindrone acetate and 5 mcg ethinyl estradiol.

Each tablet also contains the following inactive ingredients: calcium stearate, lactose monohydrate, microcrystalline cellulose, and cornstarch.

The structural formulas are as follows:

Ethinyl Estradiol [19-Norpregna-1,3,5(10)-trien-20-yne-3,17-diol, (17α)-]
Molecular Weight: 296.41
Molecular Formula: C20H24O2

Norethindrone Acetate [19-Norpregn-4-en-20-yn-3-one, 17-(acetyloxy)-, (17α)-]
Molecular Weight: 340.47
Molecular Formula: C22H28O3

CLINICAL PHARMACOLOGY

Endogenous estrogens are largely responsible for the development and maintenance of the female reproductive system and secondary sexual characteristics. Although circulating estrogens exist in a dynamic equilibrium of metabolic interconversions, estradiol is the principal intracellular human estrogen and is substantially more potent than its metabolites estrone and estriol at the receptor level.

The primary source of estrogen in normally cycling adult women is the ovarian follicle, which secretes 70 to 500 mcg of estradiol daily, depending on the phase of the menstrual cycle. After menopause, most endogenous estrogen is produced by conversion of androstenedione, secreted by the adrenal cortex, to estrone by peripheral tissues. Thus, estrone and the sulfate conjugated form, estrone sulfate, are the most abundant circulating estrogens in postmenopausal women. The pharmacologic effects of ethinyl estradiol are similar to those of endogenous estrogens.

Estrogens act through binding to nuclear receptors in estrogen-responsive tissues. To date, two estrogen receptors have been identified. These vary in proportion from tissue to tissue.

Circulating estrogens modulate the pituitary secretion of the gonadotropins, luteinizing hormone (LH) and follicle stimulating hormone (FSH) through a negative feedback mechanism. Estrogens act to reduce the elevated levels of these hormones seen in postmenopausal women.

Progestin compounds enhance cellular differentiation and generally oppose the actions of estrogens by decreasing estrogen receptor levels, increasing local metabolism of estrogens to less active metabolites, or inducing gene products that blunt cellular responses to estrogen. Progestins exert their effects in target cells by binding to specific progesterone receptors that interact with progesterone response elements in target genes. Progesterone receptors have been identified in the female reproductive tract, breast, pituitary, hypothalamus, bone, skeletal tissue and central nervous system. Progestins produce similar endometrial changes to those of the naturally occurring hormone progesterone.

Pharmacokinetics

Absorption

Norethindrone acetate (NA) is completely and rapidly deacetylated to norethindrone after oral administration, and the disposition of norethindrone acetate is indistinguishable from that of orally administered norethindrone. Norethindrone acetate and ethinyl estradiol (EE) are rapidly absorbed from femhrt tablets, with maximum plasma concentrations of norethindrone and ethinyl estradiol generally occurring 1 to 2 hours postdose. Both are subject to first-pass metabolism after oral dosing, resulting in an absolute bioavailability of approximately 64% for norethindrone and 55% for ethinyl estradiol. Bioavailability of femhrt tablets is similar to that from solution for norethindrone and slightly less for ethinyl estradiol. Administration of femhrt tablets with a high fat meal decreases rate but not extent of ethinyl estradiol absorption. The extent of norethindrone absorption is increased by 27% following administration of femhrt tablets with food.

The full pharmacokinetic profile of femhrt tablets was not characterized due to assay sensitivity limitations. However, the multiple-dose pharmacokinetics were studied at a dose of 1 mg NA/10 mcg EE in 18 post-menopausal women. Mean plasma concentrations are shown below (Figure 1) and pharmacokinetic parameters are found in Table 1. Based on a population pharmacokinetic analysis, mean steady-state concentrations of norethindrone for 1 mg NA/5 mcg EE and 1/10 are slightly more than proportional to dose when compared to 0.5 mg NA/2.5 mcg EE tablets. It can be explained by higher sex hormone binding globulin (SHBG) concentrations. Mean steady-state plasma concentrations of ethinyl estradiol for the femhrt 0.5/2.5 tablets and femhrt 1/5 tablets are proportional to dose, but there is a less than proportional increase in steady-state concentrations for the NA/EE 1/10 tablet.

Figure 1. Mean Steady-State (Day 87) Plasma Norethindrone and Ethinyl Estradiol Concentrations Following Continuous Oral Administration of 1 mg NA/10 mcg EE Tablets

Table 1.
Mean (SD) Single-Dose (Day 1) and Steady-State (Day 87) Pharmacokinetic Parameters Following Administration of 1 mg NA/10 mcg EE Tablets
 | Cmax | tmax | AUC(0-24) | CL/F | t½
Norethindrone | ng/mL | hr | ng·hr/mL | mL/min | hr
Day 1 | 6.0 (3.3) | 1.8 (0.8) | 29.7 (16.5) | 588 (416) | 10.3 (3.7)
Day 87 | 10.7 (3.6) | 1.8 (0.8) | 81.8 (36.7) | 226 (139) | 13.3 (4.5)
Ethinyl Estradiol | pg/mL | hr | pg·hr/mL | mL/min | hr
Day 1 | 33.5 (13.7) | 2.2 (1.0) | 339 (113) | ND [ND = Not determined] | ND
Day 87 | 38.3 (11.9) | 1.8 (0.7) | 471 (132) | 383 (119) | 23.9 (7.1)

Based on a population pharmacokinetic analysis, average steady-state concentrations (Css) of norethindrone and ethinyl estradiol for femhrt 1/5 tablets are estimated to be 2.6 ng/mL and 11.4 pg/mL, respectively. Css values of norethindrone and ethinyl estradiol for femhrt 0.5/2.5 tablets are estimated to be 1.1 ng/mL and 5.4 ng/mL, respectively.

The pharmacokinetics of ethinyl estradiol and norethindrone acetate were not affected by age, (age range 40-62 years), in the postmenopausal population studied.

Distribution

The distribution of exogenous estrogens is similar to that of endogenous estrogens. Estrogens are widely distributed in the body and are generally found in higher concentrations in the sex hormone target organs. Estrogens circulate in the blood largely bound to sex hormone binding globulin (SHBG) and albumin.

Volume of distribution of norethindrone and ethinyl estradiol ranges from 2 to 4 L/kg. Plasma protein binding of both steroids is extensive (>95%); norethindrone binds to both albumin and sex hormone binding globulin (SHBG), whereas ethinyl estradiol binds only to albumin. Although ethinyl estradiol does not bind to SHBG, it induces SHBG synthesis.

Metabolism

Exogenous estrogens are metabolized in the same manner as endogenous estrogens. Circulating estrogens exist in a dynamic equilibrium of metabolic interconversions. These transformations take place mainly in the liver. Estradiol is converted reversibly to estrone, and both can be converted to estriol, which is the major urinary metabolite. Estrogens also undergo enterohepatic recirculation via sulfate and glucuronide conjugation in the liver, biliary secretion of conjugates into the intestine, and hydrolysis in the gut followed by reabsorption. In postmenopausal women, a significant proportion of the circulating estrogens exist as sulfate conjugates, especially estrone sulfate, which serves as a circulating reservoir for the formation of more active estrogens.

Norethindrone undergoes extensive biotransformation, primarily via reduction, followed by sulfate and glucuronide conjugation. The majority of metabolites in the circulation are sulfates, with glucuronides accounting for most of the urinary metabolites. A small amount of norethindrone acetate is metabolically converted to ethinyl estradiol, such that exposure to ethinyl estradiol following administration of 1 mg of norethindrone acetate is equivalent to oral administration of 2.8 mcg ethinyl estradiol. Ethinyl estradiol is also extensively metabolized, both by oxidation and by conjugation with sulfate and glucuronide. Sulfates are the major circulating conjugates of ethinyl estradiol and glucuronides predominate in urine. The primary oxidative metabolite is 2-hydroxy ethinyl estradiol, formed by the CYP3A4 isoform of cytochrome P450. Part of the first-pass metabolism of ethinyl estradiol is believed to occur in gastrointestinal mucosa. Ethinyl estradiol may undergo enterohepatic circulation.

Excretion

Estradiol, estrone, and estriol are excreted in the urine along with glucuronide and sulfate conjugates.

Norethindrone and ethinyl estradiol are excreted in both urine and feces, primarily as metabolites. Plasma clearance values for norethindrone and ethinyl estradiol are similar (approximately 0.4 L/hr/kg). Steady-state elimination half-lives of norethindrone and ethinyl estradiol following administration of 1 mg NA/10 mcg EE tablets are approximately 13 hours and 24 hours, respectively.

Special Populations

Pediatric

femhrt is not indicated in children.

Geriatrics

The pharmacokinetics of femhrt have not been studied in a geriatric population.

Race

The effect of race on the pharmacokinetics of femhrt has not been studied.

Patients with Renal Insufficiency

The effect of renal disease on the disposition of femhrt has not been evaluated. In premenopausal women with chronic renal failure undergoing peritoneal dialysis who received multiple doses of an oral contraceptive containing ethinyl estradiol and norethindrone, plasma ethinyl estradiol concentrations were higher and norethindrone concentrations were unchanged compared to concentrations in premenopausal women with normal renal function (see PRECAUTIONS, Fluid Retention).

Patients with Hepatic Impairment

The effect of hepatic disease on the disposition of femhrt has not been evaluated. However, ethinyl estradiol and norethindrone may be poorly metabolized in patients with impaired liver function (see PRECAUTIONS).

Drug Interactions

See PRECAUTIONS, Drug Interactions.

In vitro and in vivo studies have shown that estrogens are metabolized partially by cytochrome P450 3A4 (CYP3A4). Therefore, inducers or inhibitors of CYP3A4 may affect estrogen drug metabolism. Inducers of CYP3A4 such as St. John’s Wort preparations (Hypericum perforatum), phenobarbital, carbamazepine, and rifampin may reduce plasma concentrations of estrogens, possibly resulting in a decrease in therapeutic effects and/or changes in the uterine bleeding profile. Inhibitors of CYP3A4 such as erythromycin, clarithromycin, ketoconazole, itraconazole, ritonavir and grapefruit juice may increase plasma concentrations of estrogens and may result in side effects.

Clinical Studies

Effects on Vasomotor Symptoms

A 12-week placebo-controlled, multicenter, randomized clinical trial was conducted in 266 symptomatic women who had at least 56 moderate to severe hot flushes during the week prior to randomization. On average, patients had 12 hot flushes per day upon study entry.

A total of 66 women were randomized to receive femhrt 1/5, 67 women were randomized to receive femhrt 0.5/2.5 and 66 women were randomized to the placebo group. femhrt 1/5 and femhrt 0.5/2.5 were shown to be statistically better than placebo at weeks 4 and 12 for relief of the frequency of moderate to severe vasomotor symptoms. See Table 2. In Table 3, femhrt 1/5 was shown to be statistically better than placebo at weeks 4 and 12 for relief of the severity of moderate to severe vasomotor symptoms; femhrt 0.5/2.5 was shown to be statistically better than placebo at weeks 5 and 12 for relief of the severity of moderate to severe vasomotor symptoms.

Table 2.
Mean Change from Baseline in the Number of Moderate to Severe Vasomotor Symptoms per Week - ITT Population, LOCF
Visit | Placebo; (N = 66) | femhrt; 0.5/2.5; (N = 67) | femhrt; 1/5; (N = 66)
Baseline [1]
Mean (SD) | 76.5 (21.4) | 77.6 (26.5) | 70.0 (16.6)
Week 4
Mean (SD) | 39.4 (27.6) | 30.2 (26.1) | 20.4 (22.7)
Mean Change from Baseline (SD) | -37.0 (26.6) | -47.4 [Denotes statistical significance at the 0.05 level] (26.1) | -49.6 (22.1)
p-Value vs. Placebo (95% CI) [2] |  | 0.041 (-20.0, -1.0) | <0.001 (-22.0,-6.0)
Week 12
Mean (SD) | 31.1 (27.0) | 13.8 (20.4) | 11.3 (18.9)
Mean Change from Baseline (SD) | -45.3 (30.2) | -63.8 (27.5) | -58.7 (23.1)
p-Value vs. Placebo (95% CI) [2] |  | <0.001 (-27.0, -7.0) | <0.001 (-25.0, -5.0)
[1] The baseline number of moderate to severe vasomotor symptoms (MSVS) is the weekly average number of MSVS during the two week prerandomization observation period.
[2] ANCOVA - Analysis of Covariance model where the observation variable is change from baseline; independent variables include treatment, center and baseline as covariate. The 95% CI - Mann-Whitney confidence interval for the difference between means (not stratified by center).
ITT = intent to treat; LOCF = last observation carried forward; CI = confidence interval
2 randomized subjects (1 in Placebo and 1 in femhrt) did not return diaries.

Table 3.
Mean Change from Baseline in the Daily Severity Score of Moderate to Severe Vasomotor Symptoms per Week - ITT Population, LOCF
Visit | Placebo; (N = 66) | femhrt; 0.5/2.5; (N = 67) | femhrt; 1/5; (N = 66)
Baseline [1]
Mean (SD) | 2.49 (0.26) | 2.48 (0.22) | 2.47 (0.23)
Week 4
Mean (SD) | 2.13 (0.74) | 1.88 (0.89) | 1.45 (1.03)
Mean Change from Baseline (SD) | -0.36 (0.68) | -0.59 (0.83) | -1.02 [Denotes statistical significance at the 0.05 level] (1.06)
p-Value vs. Placebo (95% CI) [2] | - | 0.130 (-0.3, 0.0) | <0.001 (-0.9, -0.2)
Week 5
Mean (SD) | 2.06 (0.79) | 1.68 (0.99) | 1.23 (1.03)
Mean Change from Baseline (SD) | -0.44 (0.74) | -0.80 (0.94) | -1.24 (1.07)
p-Value vs. Placebo (95% CI) [2] | - | 0.041 (-0.4, -0.0) | <0.001 (-1.2, -0.3)
Week 12
Mean (SD) | 1.82 (1.03) | 1.22 (1.11) | 1.02 (1.16)
Mean Change from Baseline (SD) | -0.67 (1.02) | -1.26 (1.08) | -1.45 (1.19)
p-Value vs. Placebo (95% CI) [2] | - | 0.002 (-0.9, -0.2) | <0.001 (-1.4, -0.3)
[1] The baseline severity of moderate to severe vasomotor symptoms (MSVS) is the daily severity score of MSVS during the two week prerandomization observation period.
[2] ANCOVA - Analysis of Covariance model where the observation variable is change from baseline; independent variables include treatment, center and baseline as covariate. The 95% CI - Mann-Whitney confidence interval for the difference between means (not stratified by center).
ITT = intent to treat; LOCF = last observation carried forward; CI = confidence interval
2 randomized subjects (1 in Placebo and 1 in femhrt) did not return diaries.

Endometrial Hyperplasia

A 2-year, placebo-controlled, multicenter, randomized clinical trial was conducted to determine the safety and efficacy of femhrt on maintaining bone mineral density, protecting the endometrium, and to determine effects on lipids. A total of 1265 women were enrolled and randomized to either placebo, 0.2 mg NA/1 mcg EE, femhrt 0.5/2.5, femhrt 1/5 and 1 mg NA/10 mcg EE or matching unopposed EE doses (1, 2.5, 5, or 10 mcg) for a total of 9 treatment groups. All participants received 1000 mg of calcium supplementation daily. Of the 1265 women randomized to the various treatment arms of this study, 137 were randomized to placebo, 146 to femhrt 1/5, 136 to femhrt 0.5/2.5 and 141 to EE 5 mcg and 137 to EE 2.5 mcg. Of these, 134 placebo, 143 femhrt 1/5, 136 femhrt 0.5/2.5, 139 EE 5 mcg and 137 EE 2.5 mcg had a baseline endometrial result. Baseline biopsies were classified as normal (in approximately 95% of subjects), or insufficient tissue (in approximately 5% of subjects). Follow-up biopsies were obtained in approximately 70-80% of patients in each arm after 12 and 24 months of therapy. Results are shown in Table 4.

Table 4.
Endometrial Biopsy Results After 12 and 24 Months of Treatment (CHART Study, 376-359)
Endometrial Status | Placebo | femhrt |  |  | EE Alone
 |  | 0.5/2.5 | 1/5 |  | 2.5 µg | 5 µg
Number of Patients Biopsied at Baseline | N = 134 | N = 136 | N = 143 |  | N = 137 | N = 139
MONTH 12 (% Patients)
Patients Biopsied (%) | 113 (84) | 103 (74) | 110 (77) |  | 100 (73) | 114 (82)
Insufficient Tissue | 30 | 34 | 45 |  | 20 | 20
Atrophic Tissue | 60 | 41 | 41 |  | 15 | 2
Proliferative Tissue | 23 | 28 | 24 |  | 65 | 91
Endometrial Hyperplasia [All patients with endometrial hyperplasia were carried forward for all time points] | 0 | 0 | 0 |  | 0 | 1
MONTH 24 (% Patients)
Patients Biopsied (%) | 94 (70) | 99 (73) | 102 (71) |  | 89 (65) | 107 (77)
Insufficient Tissue | 35 | 42 | 37 |  | 23 | 17
Atrophic Tissue | 38 | 30 | 33 |  | 6 | 2
Proliferative Tissue | 20 | 27 | 32 |  | 60 | 86
Endometrial Hyperplasia | 1 | 0 | 0 |  | 0 | 2

Irregular Bleeding/Spotting

The cumulative incidence of amenorrhea, defined as no bleeding or spotting obtained from subject recall, was evaluated over 12 months for femhrt 0.5/2.5, femhrt 1/5 and placebo arms. Results are shown in Figure 2.

Effect on Bone Mineral Density

In the 2 year study, trabecular bone mineral density (BMD) was assessed at lumbar spine using quantitative computed tomography. A total of 419 postmenopausal primarily Caucasian women, aged 40 to 64 years, with intact uteri and non-osteoporotic bone mineral densities were randomized (1:1:1) to femhrt 1/5, femhrt 0.5/2.5 or placebo. Approximately 75% of the subjects in each group completed the two-year study. All patients received 1000 mg calcium in divided doses. Vitamin D was not supplemented.

As shown in Figure 3, women treated with femhrt 1/5 had an average increase of 3.1% in lumbar spine BMD from baseline to Month 24. Women treated with femhrt 0.5/2.5 and placebo had average decreases of –0.8% and –6.3%, respectively, in spinal BMD from baseline to Month 24. The differences in the changes from baseline to Month 24 in the two femhrt groups compared with the placebo group were statistically significant.

Figure 3.

*It should be noted that when measured by QCT, BMD gains and losses are greater than when measured by dual X-ray absorptiometry (DXA). Therefore, the differences in the changes in BMD between the placebo and active drug treated groups will be larger when measured by QCT compared with DXA. Changes in BMD measured by DXA should not be compared with changes in BMD measured by QCT.

Women’s Health Initiative Studies

The Women’s Health Initiative (WHI) enrolled a total of 27,000 predominantly healthy postmenopausal women to assess the risks and benefits of either the use of oral 0.625 mg conjugated estrogens (CE) per day alone or the use of oral 0.625 mg conjugated estrogens plus 2.5 mg medroxyprogesterone acetate (MPA) per day compared to placebo in the prevention of certain chronic diseases. The primary endpoint was the incidence of coronary heart disease (CHD) (nonfatal myocardial infarction and CHD death), with invasive breast cancer as the primary adverse outcome studied. A “global index” included the earliest occurrence of CHD, invasive breast cancer, stroke, pulmonary embolism (PE), endometrial cancer, colorectal cancer, hip fracture, or death due to other cause. The study did not evaluate the effects of CE or CE/MPA on menopausal symptoms.

The CE/MPA substudy was stopped early because, according to the predefined stopping rule, the increased risk of breast cancer and cardiovascular events exceeded the specified benefits included in the “global index”. Results of the CE/MPA substudy, which included 16,608 women (average age of 63 years, range 50 to 79; 83.9% White, 6.5% Black, 5.5% Hispanic), after an average follow-up of 5.2 years are presented in Table 5 below:

Table 5.
RELATIVE AND ABSOLUTE RISK SEEN IN THE CE/MPA SUBSTUDY OF WHI
Event [a subset of the events was combined in a “global index”, defined as the earliest occurrence of CHD events, invasive breast cancer, stroke, pulmonary embolism, endometrial cancer, colorectal cancer, hip fracture, or death due to other causes] | Relative Risk CE/MPA vs placebo at 5.2 Years; (95% CI) | Placebo n = 8102 | CE/MPA; n = 8506
Event [a subset of the events was combined in a “global index”, defined as the earliest occurrence of CHD events, invasive breast cancer, stroke, pulmonary embolism, endometrial cancer, colorectal cancer, hip fracture, or death due to other causes] | Relative Risk CE/MPA vs placebo at 5.2 Years; (95% CI) | Absolute Risk per 10,000 Women-years
CHD events | 1.29 (1.02-1.63) | 30 | 37
Non-fatal MI | 1.32 (1.02-1.72) | 23 | 30
CHD death | 1.18 (0.70-1.97) | 6 | 7
Invasive breast cancer | 1.26 (1.00-1.59) | 30 | 38
Stroke | 1.41 (1.07-1.85) | 21 | 29
Pulmonary embolism | 2.13 (1.39-3.25) | 8 | 16
Colorectal cancer | 0.63 (0.43-0.92) | 16 | 10
Endometrial cancer | 0.83 (0.47-1.47) | 6 | 5
Hip fracture | 0.66 (0.45-0.98) | 15 | 10
Death due to causes other than the events above | 0.92 (0.74-1.14) | 40 | 37
Global Index | 1.15 (1.03-1.28) | 151 | 170
Deep vein thrombosis [not included in Global Index] | 2.07 (1.49-2.87) | 13 | 26
Vertebral fractures | 0.66 (0.44-0.98) | 15 | 9
Other osteoporotic fractures | 0.77 (0.69-0.86) | 170 | 131

For those outcomes included in the "global index", the absolute excess risks per 10,000 women-years in the group treated with CE/MPA were 7 more CHD events, 8 more strokes, 8 more PEs, and 8 more invasive breast cancers, while the absolute risk reductions per 10,000 women-years were 6 fewer colorectal cancers and 5 fewer hip fractures. The absolute excess risk of events included in the “global index” was 19 per 10,000 women-years. There was no difference between the groups in terms of all-cause mortality. (See BOXED WARNING, WARNINGS, and PRECAUTIONS.)

Women’s Health Initiative Memory Study

The Women’s Health Initiative Memory Study (WHIMS), a substudy of WHI, enrolled 4,532 predominantly healthy postmenopausal women 65 years of age and older (47% were age 65 to 69 years, 35% were 70 to 74 years, and 18% were 75 years of age and older) to evaluate the effects of CE/MPA (0.625 mg conjugated estrogens plus 2.5 mg medroxyprogesterone acetate) on the incidence of probable dementia (primary outcome) compared with placebo.

After an average follow-up of 4 years, 40 women in the estrogen/progestin group (45 per 10,000 women-years) and 21 in the placebo group (22 per 10,000 women-years) were diagnosed with probable dementia. The relative risk of probable dementia in the hormone therapy group was 2.05 (95% CI, 1.21 to 3.48) compared to placebo. Differences between groups became apparent in the first year of treatment. It is unknown whether these findings apply to younger postmenopausal women. (See BOXED WARNING and WARNINGS, Dementia.)

INDICATIONS AND USAGE

femhrt is indicated in women with an intact uterus for the:

1. Treatment of moderate to severe vasomotor symptoms associated with the menopause.
2. Prevention of postmenopausal osteoporosis. When prescribing solely for the prevention of postmenopausal osteoporosis, therapy should only be considered for women at significant risk of osteoporosis. Non-estrogen medications should be carefully considered.

The mainstays for decreasing the risk of postmenopausal osteoporosis are weight-bearing exercise, adequate calcium and vitamin D intake, and when indicated, pharmacologic therapy. Postmenopausal women require an average of 1500 mg/day of elemental calcium. Therefore, when not contraindicated, calcium supplementation may be helpful for women with suboptimal dietary intake. Vitamin D supplementation of 400-800 IU/day may also be required to ensure adequate daily intake in postmenopausal women.

Risk factors for osteoporosis include low bone mineral density, low estrogen levels, family history of osteoporosis, previous fracture, small frame (low BMI), light skin color, smoking, and alcohol intake. Response to therapy can be predicted by pre-treatment serum estradiol, and can be assessed during treatment by measuring biochemical markers of bone formation/resorption, and/or bone mineral density.

Estrogen therapy reduces bone resorption and retards or halts postmenopausal bone loss. Studies have shown a risk ratio of about 0.4 for hip and wrist fractures in women whose estrogen therapy was begun within a few years of menopause, compared to women taking calcium and vitamin D alone. Studies also suggest that estrogen reduces the rate of vertebral fractures. Even when started as late as 6 years after menopause, estrogen reduces further loss of bone mass for as long as treatment is continued. When estrogen therapy is discontinued, bone mass declines at a rate comparable to the immediate postmenopausal period.

Data from the Women's Health Initiative study showed that use of estrogen-plus-progestin (dose equivalent to 0.625 mg CE and 2.5 mg MPA) resulted in about 5 less hip fractures per 10,000 women-years, compared to use of placebo (risk ratio about 0.66).

CONTRAINDICATIONS

femhrt should not be used in women with any of the following conditions:

1. Undiagnosed abnormal genital bleeding.

2. Known, suspected, or history of cancer of the breast.

3. Known or suspected estrogen-dependent neoplasia.

4. Active deep vein thrombosis, pulmonary embolism or history of these conditions.

5. Active or recent (e.g., within past year) arterial thromboembolic disease (e.g., stroke, myocardial infarction).

6. Liver dysfunction or disease.

7. femhrt should not be used in patients with known hypersensitivity to its ingredients.

8. Known or suspected pregnancy. There is no indication for femhrt in pregnancy. There appears to be little or no increased risk of birth defects in children born to women who have used estrogens and progestins from oral contraceptives inadvertently during early pregnancy. (See PRECAUTIONS.)

WARNINGS

See BOXED WARNING

1. Cardiovascular disorders

Estrogen and estrogen/progestin therapy has been associated with an increased risk of cardiovascular events such as myocardial infarction and stroke, as well as venous thrombosis and pulmonary embolism (venous thromboembolism or VTE). Should any of these occur or be suspected, estrogen/progestin therapy should be discontinued immediately.

Risk factors for arterial vascular disease (e.g., hypertension, diabetes mellitus, tobacco use, hypercholesterolemia, and obesity) and/or venous thromboembolism (e.g., personal history or family history of VTE, obesity, and systemic lupus erythematosus) should be managed appropriately.

a. Coronary heart disease and stroke

In the Women’s Health Initiative (WHI) study, an increase in the number of strokes was observed in women receiving CE compared to placebo.

In the CE/MPA substudy of WHI, an increased risk of coronary heart disease (CHD) events (defined as non-fatal myocardial infarction and CHD death) was observed in women receiving CE/MPA compared to women receiving placebo (37 vs 30 per 10,000 women-years). The increase in risk was observed in year one and persisted. (See CLINICAL PHARMACOLOGY, Clinical Studies.)

In the same substudy of WHI, an increased risk of stroke was observed in women receiving CE/MPA compared to women receiving placebo (29 vs 21 per 10,000 women-years). The increase in risk was observed after the first year and persisted. (See CLINICAL PHARMACOLOGY, Clinical Studies.)

In postmenopausal women with documented heart disease (n = 2,763, average age 66.7 years) a controlled clinical trial of secondary prevention of cardiovascular disease (Heart and Estrogen/Progestin Replacement Study; HERS) treatment with CE/MPA -0.625 mg/2.5 mg per day demonstrated no cardiovascular benefit. During an average follow-up of 4.1 years, treatment with CE/MPA did not reduce the overall rate of CHD events in postmenopausal women with established coronary heart disease. There were more CHD events in the CE/MPA-treated group than in the placebo group in year 1, but not during the subsequent years. Two thousand three hundred and twenty one women from the original HERS trial agreed to participate in an open label extension of HERS, HERS II. Average follow-up in HERS II was an additional 2.7 years, for a total of 6.8 years overall. Rates of CHD events were comparable among women in the CE/MPA group and the placebo group in HERS, HERS II, and overall.

Large doses of estrogen (5 mg conjugated estrogens per day), comparable to those used to treat cancer of the prostate and breast, have been shown in a large prospective clinical trial in men to increase the risks of nonfatal myocardial infarction, pulmonary embolism, and thrombophlebitis.

b. Venous thromboembolism (VTE)

In the Women’s Health Initiative (WHI) study, an increase in VTE was observed in women receiving CE compared to placebo.

In the CE/MPA substudy of WHI, a 2-fold greater rate of VTE, including deep venous thrombosis and pulmonary embolism, was observed in women receiving CE/MPA compared to women receiving placebo. The rate of VTE was 34 per 10,000 women-years in the CE/MPA group compared to 16 per 10,000 women-years in the placebo group. The increase in VTE risk was observed during the first year and persisted. (See CLINICAL PHARMACOLOGY, Clinical Studies.)

If feasible, estrogens should be discontinued at least 4-6 weeks before surgery of the type associated with an increased risk of thromboembolism, or during periods of prolonged immobilization.

2. Malignant Neoplasms

a. Breast cancer

The use of estrogens and progestins by postmenopausal women has been reported to increase the risk of breast cancer. The most important randomized clinical trial providing information about this issue is the Women’s Health Initiative (WHI) substudy of CE/MPA (See CLINICAL PHARMACOLOGY, Clinical Studies). The results from observational studies are generally consistent with those of the WHI clinical trial and report no significant variation in the risk of breast cancer among different estrogens or progestins, doses, or routes of administration.

The CE/MPA substudy of WHI reported an increased risk of breast cancer in women who took CE/MPA for a mean follow-up of 5.6 years. Observational studies have also reported an increased risk for estrogen/progestin combination therapy, and a smaller increased risk for estrogen-alone therapy, after several years of use. In the WHI trial and from observational studies, the excess risk increased with duration of use. From observational studies, the risk appeared to return to baseline in about five years after stopping treatment. In addition, observational studies suggest that the risk of breast cancer was greater, and became apparent earlier, with estrogen/progestin combination therapy as compared to estrogen-alone therapy.

In the CE/MPA substudy, 26% of the women reported prior use of estrogen-alone and/or estrogen/progestin combination hormone therapy. After a mean follow-up of 5.6 years during the clinical trial, the overall relative risk of invasive breast cancer was 1.24 (95% confidence interval 1.01-1.54), and the overall absolute risk was 41 vs 33 cases per 10,000 women-years, for CE/MPA compared with placebo. Among women who reported prior use of hormone therapy, the relative risk of invasive breast cancer was 1.86, and the absolute risk was 46 vs 25 cases per 10,000 women-years, for CE/MPA compared with placebo. Among women who reported no prior use of hormone therapy, the relative risk of invasive breast cancer was 1.09, and the absolute risk was 40 vs 36 cases per 10,000 women-years for CE/MPA compared with placebo. In the same substudy, invasive breast cancers were larger and diagnosed at a more advanced stage in the CE/MPA group compared with the placebo group. Metastatic disease was rare with no apparent difference between the two groups. Other prognostic factors such as histologic subtype, grade and hormone receptor status did not differ between the groups.

The use of estrogen-plus-progestin has been reported to result in an increase in abnormal mammograms requiring further evaluation. All women should receive yearly breast examinations by a healthcare provider and perform monthly breast self-examinations. In addition, mammography examinations should be scheduled based on patient age, risk factors, and prior mammogram results.

b. Endometrial cancer

The use of unopposed estrogens in women with intact uteri has been associated with an increased risk of endometrial cancer. The reported endometrial cancer risk among unopposed estrogen users is about 2- to 12-fold greater than in non-users, and appears dependent on duration of treatment and on estrogen dose. Most studies show no significant increased risk associated with use of estrogens for less than one year. The greatest risk appears associated with prolonged use, with increased risks of 15- to 24-fold for five to ten years or more and this risk has been shown to persist for at least 8 to 15 years after estrogen therapy is discontinued.

Clinical surveillance of all women taking estrogen/progestin combinations is important. Adequate diagnostic measures, including endometrial sampling when indicated, should be undertaken to rule out malignancy in all cases of undiagnosed persistent or recurring abnormal vaginal bleeding. There is no evidence that the use of natural estrogens results in a different endometrial risk profile than synthetic estrogens of equivalent estrogen dose. Adding a progestin to estrogen therapy has been shown to reduce the risk of endometrial hyperplasia, which may be a precursor to endometrial cancer.

3. Dementia

In the Women’s Health Initiative Memory Study (WHIMS), 4,532 generally healthy postmenopausal women 65 years of age and older were studied, of whom 35% were 70 to 74 years of age and 18% were 75 or older. After an average follow-up of 4 years, 40 women being treated with CE/MPA (1.8%, n = 2,229) and 21 women in the placebo group (0.9%, n = 2,303) received diagnoses of probable dementia. The relative risk for CE/MPA versus placebo was 2.05 (95% confidence interval 1.21 – 3.48), and was similar for women with and without histories of menopausal hormone use before WHIMS. The absolute risk of probable dementia for CE/MPA versus placebo was 45 versus 22 cases per 10,000 women-years, and the absolute excess risk for CE/MPA was 23 cases per 10,000 women-years. It is unknown whether these findings apply to younger postmenopausal women. (See CLINICAL PHARMACOLOGY, Clinical Studies and PRECAUTIONS, Geriatric Use.)

4. Gallbladder Disease

A 2- to 4-fold increase in the risk of gallbladder disease requiring surgery in women receiving postmenopausal estrogen has been reported.

5. Hypercalcemia

Estrogen administration may lead to severe hypercalcemia in patients with breast cancer and bone metastases. If hypercalcemia occurs, use of the drug should be stopped and appropriate measures taken to reduce the serum calcium level.

6. Visual Abnormalities

Retinal vascular thrombosis has been reported in patients receiving estrogens. Discontinue medication pending examination if there is sudden partial or complete loss of vision, or a sudden onset of proptosis, diplopia, or migraine. If examination reveals papilledema or retinal vascular lesions, estrogens should be permanently discontinued.

PRECAUTIONS

A. General

1. Addition of a progestin when a woman has not had a hysterectomy

A daily dose of femhrt contains a progestin.

Studies of the addition of a progestin for 10 or more days of a cycle of estrogen administration, or daily with estrogen in a continuous regimen, have reported a lowered incidence of endometrial hyperplasia than would be induced by estrogen treatment alone. Endometrial hyperplasia may be a precursor to endometrial cancer.

There are, however, possible risks that may be associated with the use of progestins with estrogens compared to estrogen-alone treatment. These include a possible increased risk of breast cancer.

2. Elevated blood pressure

In a small number of case reports, substantial increases in blood pressure have been attributed to idiosyncratic reactions to estrogens. In a large, randomized, placebo-controlled clinical trial, a generalized effect of estrogens on blood pressure was not seen. Blood pressure should be monitored at regular intervals with estrogen use.

3. Hypertriglyceridemia

In patients with pre-existing hypertriglyceridemia, estrogen therapy may be associated with elevations of plasma triglycerides leading to pancreatitis and other complications.

4. Impaired liver function and past history of cholestatic jaundice

Estrogens may be poorly metabolized in patients with impaired liver function. For patients with a history of cholestatic jaundice associated with past estrogen use or with pregnancy, caution should be exercised and in the case of recurrence, medication should be discontinued.

5. Hypothyroidism

Estrogen administration leads to increased thyroid-binding globulin (TBG) levels. Patients with normal thyroid function can compensate for the increased TBG by making more thyroid hormone, thus maintaining free T4 and T3 serum concentrations in the normal range. Patients dependent on thyroid hormone replacement therapy who are also receiving estrogens may require increased doses of their thyroid replacement therapy. These patients should have their thyroid function monitored in order to maintain their free thyroid hormone levels in an acceptable range.

6. Fluid retention

Because estrogens may cause some degree of fluid retention, patients with conditions that might be influenced by this factor, such as a cardiac or renal dysfunction, warrant careful observation when estrogens are prescribed.

7. Hypocalcemia

Estrogens should be used with caution in individuals with severe hypocalcemia.

8. Ovarian cancer

The CE/MPA substudy of WHI reported that estrogen-plus-progestin increased the risk of ovarian cancer. After an average follow-up of 5.6 years, the relative risk for ovarian cancer for CE/MPA versus placebo was 1.58 (95% confidence interval 0.77 – 3.24) but was not statistically significant. The absolute risk for CE/MPA versus placebo was 4.2 versus 2.7 cases per 10,000 women-years. In some epidemiologic studies, the use of estrogen-alone, in particular for ten or more years, has been associated with an increased risk of ovarian cancer. Other epidemiologic studies have not found these associations.

9. Exacerbation of endometriosis

Endometriosis may be exacerbated with administration of estrogens. A few cases of malignant transformation of residual endometrial implants have been reported in women treated post-hysterectomy with estrogen alone therapy. For patients known to have residual endometriosis post-hysterectomy, the addition of progestin should be considered.

10. Exacerbation of other conditions

Estrogens may cause an exacerbation of asthma, diabetes mellitus, epilepsy, migraine or porphyria, systemic lupus erythematosus, and hepatic hemangiomas and should be used with caution in women with these conditions.

B. PATIENT INFORMATION

Physicians are advised to discuss the PATIENT INFORMATION leaflet with patients for whom they prescribe femhrt.

See text of Patient Information which appears after the HOW SUPPLIED section.

C. LABORATORY TESTS

Estrogen administration should be initiated at the lowest dose approved for the indication and then guided by clinical response rather than by serum hormone levels (e.g., estradiol, FSH).

D. DRUG/LABORATORY TEST INTERACTIONS

The following drug/laboratory interactions have been observed with estrogen therapy, and/or femhrt:

1. In a 12-week study, femhrt 0.5/2.5 and femhrt 1/5 decreased Factor VII, and femhrt 1/5 decreased plasminogen activator inhibitor-1 from baseline in a dose-related manner but remained within the laboratory reference range for postmenopausal women. Mean levels of fibrinogen and partial thromboplastin time changed minimally from baseline for femhrt 0.5/2.5 and femhrt 1/5.
2. Estrogen therapy may increase thyroxine-binding globulin (TBG), leading to increased circulating total thyroid hormone (T4) as measured by protein-bound iodine (PBI), T4 levels (by column or radioimmunoassay), or T3 levels by radioimmunoassay. T3 resin uptake is decreased, reflecting the elevated TBG. Free T4 and free T3 concentrations are unaltered. Patients on thyroid replacement therapy may require higher doses of thyroid hormone.
3. Estrogen therapy may elevate other binding proteins in serum, i.e., corticosteroid binding globulin (CBG), sex hormone binding globulin (SHBG), leading to increased circulating corticosteroids and sex steroids, respectively. Free hormone concentrations may be decreased. Other plasma proteins may be increased (angiotensinogen/renin substrate, alpha-1-antitrypsin, ceruloplasmin).
  femhrt 0.5/2.5 and femhrt 1/5 were associated with an SHBG increase of 15% and 22%, respectively.
4. Estrogen therapy increases plasma HDL and HDL2 subfraction concentrations, reduces LDL cholesterol concentration and increases triglyceride levels.
5. Estrogen therapy is associated with impaired glucose tolerance.
6. Estrogen therapy reduces response to metyrapone test.

E. Drug/Drug Interactions

No drug-drug interaction studies have been conducted with femhrt.

In vitro and in vivo studies have shown that estrogens are metabolized partially by cytochrome P450 3A4 (CYP3A4). Therefore, inducers or inhibitors of CYP3A4 may affect estrogen drug metabolism. Inducers of CYP3A4 such as St. John’s Wort preparations (Hypericum perforatum), phenobarbital, carbamazepine, and rifampin may reduce plasma concentrations of estrogens, possibly resulting in a decrease in therapeutic effects and/or changes in the uterine bleeding profile. Inhibitors of CYP3A4 such as erythromycin, clarithromycin, ketoconazole, intraconazole, ritonavir and grapefruit juice may increase plasma concentrations of estrogens and may result in side effects.

The following section contains information on drug interactions with ethinyl estradiol-containing products (specifically, oral contraceptives) that have been reported in the public literature. It is unknown whether such interactions occur with femhrt or drug products containing other types of estrogens.

The Effect of Ethinyl Estradiol on Other Drugs

Drug products containing ethinyl estradiol may inhibit the metabolism of other compounds. Increased plasma concentrations of cyclosporin, prednisolone, and theophylline have been reported with concomitant administration of certain drugs containing ethinyl estradiol (e.g., oral contraceptives containing ethinyl estradiol). In addition, drugs containing ethinyl estradiol may induce the conjugation of other compounds.

Decreased plasma concentrations of acetaminophen and increased clearance of temazapam, salicylic acid, morphine, and clofibric acid have been noted when these drugs were administered with certain ethinyl estradiol-containing drug products (e.g., oral contraceptives containing ethinyl estradiol).

F. CARCINOGENESIS, MUTAGENESIS, IMPAIRMENT OF FERTILITY

Long-term continuous administration of estrogen, with and without progestin, in women with and without a uterus, has shown an increased risk of endometrial cancer, breast cancer, and ovarian cancer. (See BOXED WARNING, WARNINGS and PRECAUTIONS.)

Long-term continuous administration of natural and synthetic estrogens in certain animal species increases the frequency of carcinomas of the breast, uterus, cervix, vagina, testis, and liver.

G. PREGNANCY

femhrt should not be used during pregnancy. (See CONTRAINDICATIONS.)

H. NURSING MOTHERS

Estrogen administration to nursing mothers has been shown to decrease the quantity and quality of the milk. Detectable amounts of drug have been identified in the milk of mothers receiving these drugs. Caution should be exercised when femhrt is administered to nursing mothers.

I. PEDIATRIC USE

femhrt is not indicated in children.

J. GERIATRIC USE

There have not been sufficient numbers of geriatric patients involved in clinical trials utilizing femhrt to determine whether those over 65 years of age differ from younger subjects in their response to femhrt.

In the Women’s Health Initiative Memory Study, including 4,532 women 65 years of age and older, followed for an average of 4 years, 82% (n = 3,729) were 65 to 74 while 18% (n = 803) were 75 and over. Most women (80%) had no prior hormone therapy use. Women treated with conjugated estrogens plus medroxyprogesterone acetate were reported to have a two-fold increase in the risk of developing probable dementia. Alzheimer’s disease was the most common classification of probable dementia in both the conjugated estrogens plus medroxyprogesterone acetate group and the placebo group. Ninety percent of the cases of probable dementia occurred in the 54% of women that were older than 70. (See WARNINGS, Dementia.)

ADVERSE REACTIONS

See BOXED WARNING, WARNINGS and PRECAUTIONS.

Because clinical trials are conducted under widely varying conditions, adverse reaction rates observed in the clinical trials of a drug cannot be directly compared to rates in the clinical trials of another drug and may not reflect the rates observed in practice. The adverse reaction information from clinical trials does, however, provide a basis for identifying the adverse events that appear to be related to drug use and for approximating rates.

Adverse events reported in controlled clinical studies of femhrt are shown in Table 6 below.

Table 6.
All Treatment-Emergent Adverse Events Reported at a Frequency of ≥5% of Patients with femhrt
BODY SYSTEM/; Adverse Event | Percent of Patients (%)
 | Placebo | femhrt 0.5/2.5 | femhrt 1/5
 | N = 247 | N = 244 | N = 258
BODY AS A WHOLE | 40.1 | 38.5 | 39.5
Headache | 14.6 | 15.2 | 18.2
Back Pain | 5.3 | 5.3 | 4.7
Viral Infection | 7.7 | 8.6 | 7.0
DIGESTIVE SYSTEM | 24.4 | 30.5 | 33.0
Nausea and/or Vomiting | 5.3 | 5.3 | 7.4
Abdominal Pain | 4.5 | 10.2 | 8.1
Dyspepsia | 2.0 | 5.3 | 3.1
Diarrhea | 3.6 | 5.7 | 3.9
MUSCULOSKELETAL SYSTEM | 21.7 | 20.3 | 20.4
Arthralgia | 6.9 | 2.9 | 5.8
Myalgia | 8.5 | 8.6 | 7.8
PSYCHOBIOLOGIC FUNCTION | 8.3 | 7.9 | 14.1
Nervousness | 1.6 | 1.6 | 5.4
Depression | 3.6 | 3.7 | 5.8
RESPIRATORY SYSTEM | 37.2 | 33.9 | 35.6
Rhinitis | 15.4 | 12.7 | 15.1
Sinusitis | 9.7 | 9.4 | 8.1
UROGENITAL SYSTEM | 25.0 | 31.6 | 40.8
Breast Pain | 5.3 | 9.0 | 8.1
Urinary Tract Infection | 3.2 | 3.7 | 6.2
Vaginitis | 4.9 | 4.5 | 5.4

The following additional adverse reactions have been reported with estrogen and/or progestin therapy.

1. Genitourinary system

Changes in vaginal bleeding pattern and abnormal withdrawal bleeding or flow; breakthrough bleeding; spotting; increase in size of uterine leiomyomata, vaginitis, including vaginal candidiasis; change in amount of cervical secretion; changes in cervical ectropion; ovarian cancer; endometrial hyperplasia; endometrial cancer.

2. Breasts

Tenderness, enlargement, pain, nipple discharge, galactorrhea; fibrocystic breast changes; breast cancer.

3. Cardiovascular

Deep and superficial venous thrombosis; pulmonary embolism; thrombophlebitis; myocardial infarction; stroke; increase in blood pressure.

4. Gastrointestinal

Nausea, vomiting; cholestatic jaundice; pancreatitis, enlargement of hepatic hemangiomas; bloating, abdominal cramps; increased incidence of gallbladder disease.

5. Skin

Chloasma or melasma that may persist when drug is discontinued; erythema multiforme; erythema nodosum; hemorrhagic eruption; loss of scalp hair; hirsutism; rash, pruritus.

6. Eyes

Retinal vascular thrombosis, intolerance to contact lenses.

7. Central nervous system

Headache; migraine; dizziness; mental depression; chorea; nervousness; mood disturbances; irritability; exacerbation of epilepsy, dementia.

8. Miscellaneous

Increase or decrease in weight; reduced carbohydrate tolerance; aggravation of porphyria; edema; arthralgias; leg cramps; changes in libido; urticaria, angioedema, anaphylactoid/anaphylactic reactions; hypocalcemia; exacerbation of asthma; increased triglycerides.

OVERDOSAGE

Serious ill effects have not been reported following acute ingestion of large doses of progestin/estrogen-containing oral contraceptives by young children. Overdosage of estrogen may cause nausea and vomiting, and withdrawal bleeding may occur.

DOSAGE AND ADMINISTRATION

Use of estrogen, alone or in combination with a progestin, should be limited to the shortest duration consistent with treatment goals and risks for the individual woman. Patients should be reevaluated periodically as clinically appropriate (e.g., 3 to 6 month intervals) to determine if treatment is still necessary (see BOXED WARNING and WARNINGS). For women who have a uterus, adequate diagnostic measures, such as endometrial sampling, when indicated, should be undertaken to rule out malignancy in cases of undiagnosed persistent or recurring abnormal vaginal bleeding. Patients should be evaluated for breast abnormalities in accordance with good clinical practice.

Patients should be started at the lowest dose.

femhrt therapy consists of a single tablet taken once daily.

1. For the Treatment of Moderate to Severe Vasomotor Symptoms associated with the menopause

femhrt should be given once daily for the treatment of moderate to severe vasomotor symptoms associated with the menopause. Patients should be reevaluated at 3 to 6 month intervals to determine if treatment is still necessary.

2. For Prevention of Postmenopausal Osteoporosis

When prescribing solely of the prevention of postmenopausal osteoporosis, femhrt should only be prescribed to postmenopausal women who are at significant risk of osteoporosis. Non-estrogen medications should be carefully considered. Risk factors for osteoporosis include low bone mineral density, low estrogen levels, family history of osteoporosis, previous fracture, small frame (low BMI), light skin color, smoking, and alcohol intake. Patients should be treated with the lowest effective dose. This dose should be periodically reassessed by the healthcare provider. Response to therapy can be assessed during treatment by measuring biochemical markers of bone formation/resorption, and/or bone mineral density.

HOW SUPPLIED

femhrt® tablets are available in the following strength and package sizes:

N 54868-4679-0 | Blister card of 28 D-shaped white tablets with 1 mg norethindrone acetate and 5 mcg ethinyl estradiol; imprinted with WC on one side and 144 on the other.

Rx only

Keep this drug and all drugs out of the reach of children.

Store at 25° C (77° F); excursions permitted to 15 - 30° C (59 - 86° F) [see USP Controlled Room Temperature].

INFORMATION FOR THE PATIENT

(Revised October 2009)

Please read this PATIENT INFORMATION before you start taking femhrt® and each time you refill femhrt. There may be new information. This information does not take the place of talking to your healthcare provider about your medical condition or your treatment.

What is the most important information I should know about femhrt (a combination of estrogen and progestin hormones)?

- Do not use estrogens and progestins to prevent heart disease, heart attacks, strokes or dementia.

Using estrogens and progestins may increase your chances of getting heart attack, strokes, breast cancer, and blood clots. Using estrogens, with or without progestins may increase your risk of dementia, based on a study of women age 65 years or older. It is unknown whether this study applies to women who began estrogen and progestin therapy before age 65. You and your healthcare provider should talk regularly about whether you still need treatment with femhrt.

What is femhrt?

femhrt is medicine that contains two kinds of hormones, an estrogen and a progestin.

What is femhrt used for?

femhrt is used after menopause to:

- reduce moderate to severe hot flushes

Estrogens are hormones made by a woman’s ovaries. The ovaries normally stop making estrogens when a woman is between 45 to 55 years old. This drop in body estrogen levels causes the “change of life” or menopause, the end of monthly menstrual periods. Sometimes both ovaries are removed during an operation before natural menopause takes place. The sudden drop in estrogen levels causes “surgical menopause”.

When estrogen levels begin dropping, some women develop very uncomfortable symptoms, such as feelings of warmth in the face, neck, and chest, or sudden intense episodes of heat and sweating (“hot flashes” or “hot flushes”). In some women the symptoms are mild; in others they can be severe. You and your healthcare provider should talk regularly about whether you still need treatment with femhrt.

- help reduce your chances of getting osteoporosis (thin, weak bones)

Osteoporosis from menopause is a thinning of the bones that makes them weaker and easier to break. If you use femhrt only to prevent osteoporosis from menopause, talk with your healthcare provider about whether a different treatment or medicine without estrogens might be better for you. You and your healthcare provider should talk regularly about whether you should continue with femhrt.

Weight-bearing exercise, like walking or running, and taking calcium and vitamin D supplements may also lower your chances of getting postmenopausal osteoporosis. It is important to talk about exercise and supplements with your healthcare provider before starting them.

Who should not take femhrt?

Do not take femhrt if you have had your uterus removed (hysterectomy).

femhrt contains a progestin to decrease the chances of getting cancer of the uterus. If you do not have a uterus, you do not need a progestin and you should not take femhrt.

Do not start taking femhrt if you:

- currently have or have had certain cancers. Estrogens may increase the chances of getting certain types of cancers, including cancer of the breast and uterus. If you have or had cancer, talk with your healthcare provider about whether you should take femhrt.
- had a stroke or heart attack in the past year.
- currently have or have had blood clots.
- currently have or have had liver problems.
- are allergic to femhrt or any of its ingredients. See the end of this leaflet for a list of ingredients in femhrt.
- think you may be pregnant. If you think you may be pregnant, do not take femhrt.

Tell your healthcare provider:

- if you are breastfeeding. The hormones in femhrt can pass into your milk.

- about all of your medical problems. Your healthcare provider may need to check you more carefully if you have certain conditions, such as asthma (wheezing), epilepsy (seizures), migraine, endometriosis, lupus, problems with your heart, liver, thyroid, kidneys, or have high calcium levels in your blood.

- about all the medicines you take, including prescription and nonprescription medicines, vitamins, and herbal supplements. Some medicines may affect how femhrt works. femhrt may also affect how your other medicines work.

- if you are going to have surgery or will be on bed rest. You may need to stop taking estrogens and progestins.

How should I take femhrt?

Take your femhrt pill once a day at about the same time each day. If you miss a dose, take it as soon as you remember. If it is almost time for your next dose, skip the missed dose and go back to your normal schedule. Do not take two doses at the same time.

Start at the lowest dose and talk to your healthcare provider about how well that dose is working for you.

Estrogens should only be used as long as needed. You and your healthcare provider should reevaluate every 3 to 6 months whether or not you still need treatment with femhrt.

What are the possible risks and side effects of femhrt?

Less common but serious side effects include:

- Breast cancer
- Cancer of the uterus
- Stroke
- Heart attack
- Blood clots
- Dementia
- Gallbladder disease
- Ovarian cancer

These are some of the warning signs of serious side effects:

- Breast lumps
- Unusual vaginal bleeding
- Dizziness and faintness
- Changes in speech
- Severe headaches
- Chest pain
- Shortness of breath
- Pains in your legs
- Changes in vision
- Vomiting

Call your healthcare provider right away if you get any of these warning signs, or any other unusual symptom that concerns you.

Common side effects include:

- Headache
- Breast pain
- Irregular vaginal bleeding or spotting
- Stomach/abdominal cramps, bloating
- Nausea and vomiting
- Hair loss

Other side effects include:

- High blood pressure
- Liver problems
- High blood sugar
- Fluid retention
- Enlargement of benign tumors of the uterus (“fibroids”)
- Vaginal yeast infection

These are not all the possible side effects of femhrt. For more information, ask your healthcare provider or pharmacist.

What can I do to lower my chances of a serious side effect with femhrt?

- Talk with your healthcare provider regularly (every 3-6 months) about whether you should continue taking femhrt.
- See your healthcare provider right away if you develop vaginal bleeding while taking femhrt.
- Have a breast exam and mammogram (breast x-ray) every year unless your healthcare provider tells you something else. If members of your family have had breast cancer or if you have ever had breast lumps or an abnormal mammogram (breast x-ray), you may need to have breast exams more often.
- If you have high blood pressure, high cholesterol (fat in the blood), diabetes, are overweight, or use tobacco, you may have higher chances for getting heart disease. Ask your healthcare provider for ways of lowering your chances for getting heart disease.

General information about safe and effective use of femhrt

Medicines are sometimes prescribed for conditions that are not mentioned in patient information leaflets. Do not take femhrt for conditions for which it was not prescribed. Do not give femhrt to other people, even if they have the same symptoms you have. It may harm them.

Keep all drugs out of the reach of children. In case of overdose, call your doctor, hospital, or poison control center right away. This leaflet provides a summary of the most important information about femhrt. If you would like more information, talk with your healthcare provider or pharmacist. You can ask for information about femhrt that is written for health professionals. You can get more information by calling the toll free number 800-521-8813.

What are the ingredients in femhrt?

Each white tablet contains norethindrone acetate and ethinyl estradiol. Each tablet also contains calcium stearate, lactose monohydrate, microcrystalline cellulose, and cornstarch.

Manufactured by:
Warner Chilcott Company, LLC
Fajardo, Puerto Rico 00738
Marketed by:
Warner Chilcott (US), LLC
Rockaway, NJ 07866
1-800-521-8813

To report SUSPECTED ADVERSE REACTIONS, contact Warner Chilcott at 1-800-521-8813 or FDA at 1-800-FDA-1088 or www.fda.gov/medwatch.

Revised October 2009 0544G282

Relabeling of "Additional" barcode label by:
Physicians Total Care, Inc.
Tulsa, OK 74146

Femhrt - 1 mg/5 mcg

Femhrt

(norethindrone acetate/ethinyl estradiol tablets)

1 mg/5 mcg

Each white D-shaped tablet contains 1 mg norethindrone acetate and 5 mcg ethinyl estradiol.

Usual Dosage - One tablet daily. See Package Insert for Full Prescribing Information.

This package is not child resistant.

Keep this and all drugs out of the reach of children.

Store at 25o C (77o F); excursions permitted to 15o - 30o C (59o- 86o F) [see USP Controlled Room Temperature].